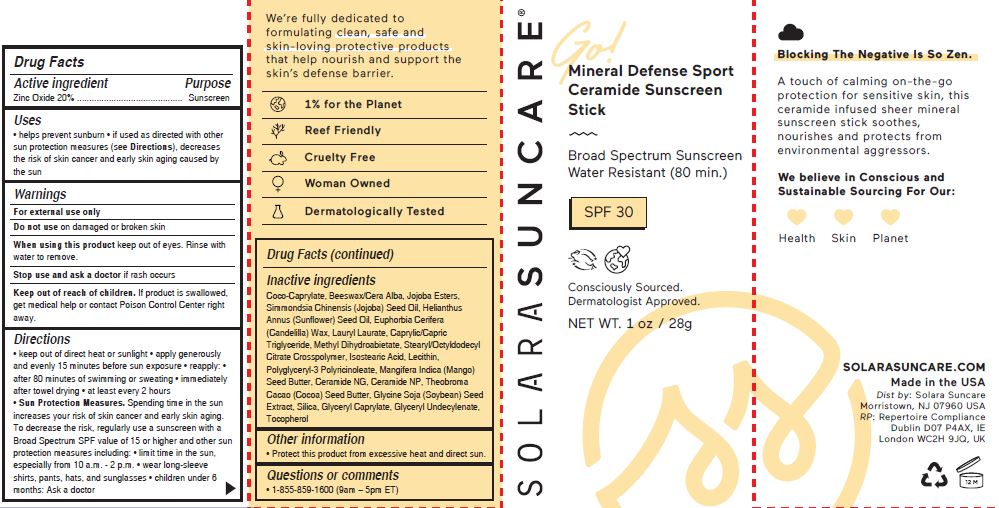 DRUG LABEL: MINERAL DEFENSE SPORT CERAMIDE

NDC: 73054-108 | Form: STICK
Manufacturer: SOLARA SUNCARE, INC.
Category: otc | Type: HUMAN OTC DRUG LABEL
Date: 20251222

ACTIVE INGREDIENTS: ZINC OXIDE 20 g/100 g
INACTIVE INGREDIENTS: LECITHIN, SUNFLOWER; POLYGLYCERYL-3 PENTARICINOLEATE; MANGIFERA INDICA SEED BUTTER; CERAMIDE NG; CERAMIDE NP; COCOA BUTTER; SOYBEAN; SILICON DIOXIDE; GLYCERYL MONOCAPRYLATE; GLYCERYL 1-UNDECYLENATE; TOCOPHEROL; COCO-CAPRYLATE; WHITE WAX; JOJOBA OIL, RANDOMIZED; SIMMONDSIA CHINENSIS SEED; HELIANTHUS ANNUUS SEED WAX; CANDELILLA WAX; LAURYL LAURATE; MEDIUM-CHAIN TRIGLYCERIDES; METHYL DIHYDROABIETATE; OCTYLDODECYL CITRATE CROSSPOLYMER; ISOSTEARIC ACID

SOLARA (as PLD) - GO! MINERAL DEFENSE SPORT CERAMIDE SUNSCREEN STICK (73054-108)

ACTIVE INGREDIENTS

Zinc Oxide 20%

PURPOSE

Sunscreen

USES

- helps prevent sunburn • if used as directed with other sun protection measures (see Directions), decreases the risk of skin cancer and early skin aging caused by the sun

Keep out of reach of children. If product is swallowed, get medical help or contact Poison Control Center right away.

Warnings

For external use only

Do not use on damaged or broken skin

When using this product keep out of eyes. Rinse with water to remove.

Stop use and ask a doctor if rash occurs

DIRECTIONS

- keep out of direct heat or sunlight
- apply generously and evenly 15 minutes before sun exposure
- reapply:
- after 80 minutes of swimming or sweating
- immediately after towel drying
- at least every 2 hours

- Sun Protection Measures. Spending time in the sun increases your risk of skin cancer and early skin aging. To decrease the risk, regularly use asunscreen with a Broad Spectrum SPF value of 15 or higher and other sun protection measures including:
- limit time in the sun, especially from 10 a.m. - 2 p.m.
- wear long-sleeve shirts, pants, hats, and sunglasses
- children under 6 months: Ask a doctor

INACTIVE INGREDIENTS

Coco-Caprylate, Beeswax/Cera Alba, Jojoba Esters, Simmondsia Chinensis (Jojoba) Seed Oil, Helianthus Annus (Sunflower) Seed Oil, Euphorbia Cerifera (Candelilla) Wax, Lauryl Laurate, Caprylic/Capric Triglyceride, Methyl Dihydroabietate, Stearyl/Octyldodecyl Citrate Crosspolymer, Isostearic Acid, Lecithin, Polyglyceryl-3 Polyricinoleate, Mangifera Indica (Mango) Seed Butter, Ceramide NG, Ceramide NP, Theobroma Cacao (Cocoa) Seed Butter, Glycine Soja (Soybean) Seed Extract, Silica, Glyceryl Caprylate, Glyceryl Undecylenate, Tocopherol

OTHER INFORMATION

- Protect this product from excessive heat and direct sun.

QUESTIONS OR COMMENTS

- 1-855-859-1600 (9am – 5pm ET)